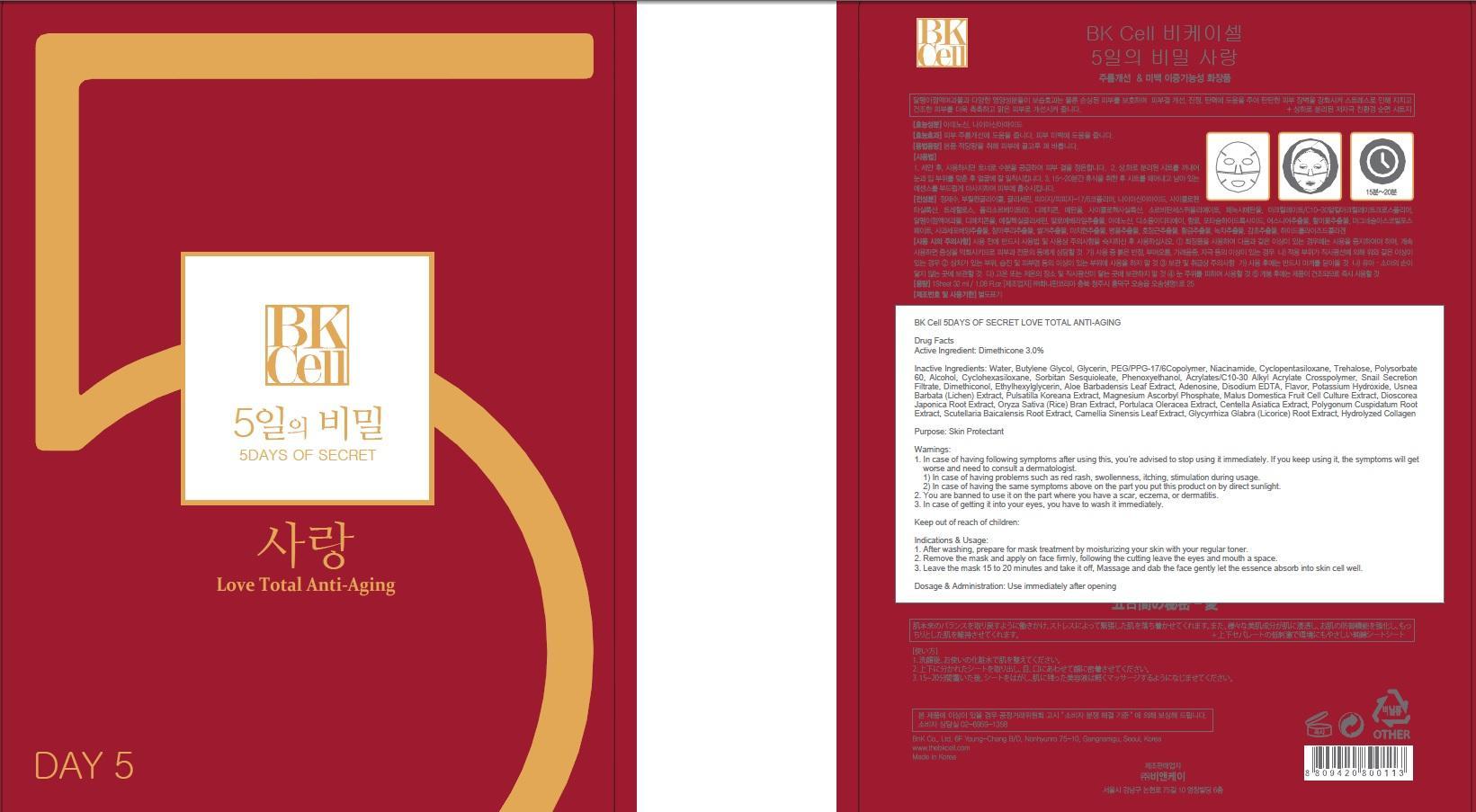 DRUG LABEL: BK Cell 5DAYS OF SECRET LOVE TOTAL ANTI AGING
NDC: 69946-050 | Form: PATCH
Manufacturer: BNK CO., LTD.
Category: otc | Type: HUMAN OTC DRUG LABEL
Date: 20150715

ACTIVE INGREDIENTS: Dimethicone 0.96 mg/32 mL
INACTIVE INGREDIENTS: Water; Butylene Glycol

ACTIVE INGREDIENT

Active Ingredient: Dimethicone 3.0%

INACTIVE INGREDIENT

Inactive Ingredients: Water, Butylene Glycol, Glycerin, PEG/PPG-17/6Copolymer, Niacinamide, Cyclopentasiloxane, Trehalose, Polysorbate 60, Alcohol, Cyclohexasiloxane, Sorbitan Sesquioleate, Phenoxyethanol, Acrylates/C10-30 Alkyl Acrylate Crosspolymer, Snail Secretion Filtrate, Dimethiconol, Ethylhexylglycerin, Aloe Barbadensis Leaf Extract, Adenosine, Disodium EDTA, Flavor, Potassium Hydroxide, Usnea Barbata (Lichen) Extract, Pulsatilla Koreana Extract, Magnesium Ascorbyl Phosphate, Malus Domestica Fruit Cell Culture Extract, Dioscorea Japonica Root Extract, Oryza Sativa (Rice) Bran Extract, Portulaca Oleracea Extract, Centella Asiatica Extract, Polygonum Cuspidatum Root Extract, Scutellaria Baicalensis Root Extract, Camellia Sinensis Leaf Extract, Glycyrrhiza Glabra (Licorice) Root Extract, Hydrolyzed Collagen

PURPOSE

Purpose: Skin Protectant

WARNINGS

Warnings: 1. In case of having following symptoms after using this, you're advised to stop using it immediately. If you keep using it, the symptoms will get worse and need to consult a dermatologist. 1) In case of having problems such as red rash, swollenness, itching, stimulation during usage. 2) In case of having the same symptoms above on the part you put this product on by direct sunlight. 2. You are banned to use it on the part where you have a scar, eczema, or dermatitis. 3. In case of getting it into your eyes, you have to wash it immediately.

KEEP OUT OF REACH OF CHILDREN

Keep out of reach of babies and children

INDICATIONS & USAGE

Indications & Usage: 1. After washing, prepare for mask treatment by moisturizing your skin with your regular toner. 2. Remove the mask and apply on face firmly, following the cutting leave the eyes and mouth a space. 3. Leave the mask 15 to 20 minutes and take it off, Massage and dab the face gently let the essence absorb into skin cell well.

DOSAGE & ADMINISTRATION

Dosage & Administration: Use immediately after opening